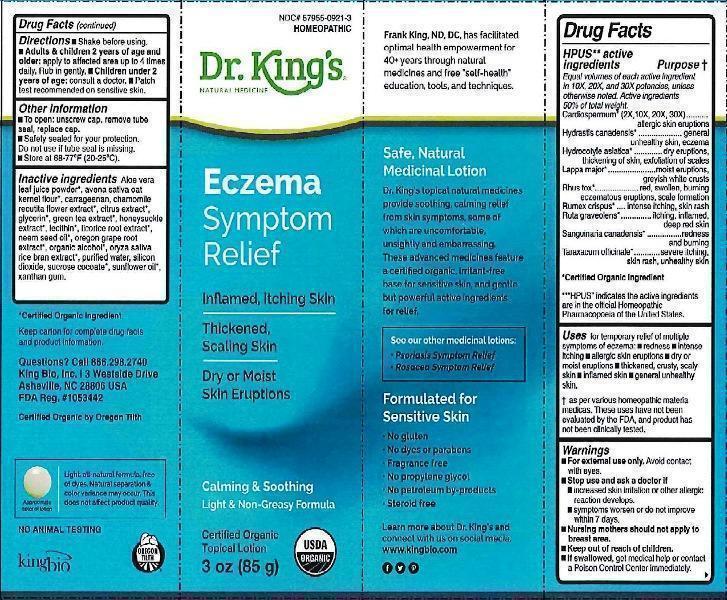 DRUG LABEL: Eczema Symptom Relief
NDC: 57955-0921 | Form: CREAM
Manufacturer: King Bio Inc.
Category: homeopathic | Type: HUMAN OTC DRUG LABEL
Date: 20170120

ACTIVE INGREDIENTS: CARDIOSPERMUM HALICACABUM FLOWERING TOP 2 [hp_X]/85 g; GOLDENSEAL 10 [hp_X]/85 g; CENTELLA ASIATICA 10 [hp_X]/85 g; ARCTIUM LAPPA ROOT 10 [hp_X]/85 g; TOXICODENDRON PUBESCENS LEAF 10 [hp_X]/85 g; RUMEX CRISPUS ROOT 10 [hp_X]/85 g; RUTA GRAVEOLENS FLOWERING TOP 10 [hp_X]/85 g; SANGUINARIA CANADENSIS ROOT 10 [hp_X]/85 g; TARAXACUM OFFICINALE 10 [hp_X]/85 g
INACTIVE INGREDIENTS: ALOE VERA LEAF; OATMEAL; CHONDRUS CRISPUS CARRAGEENAN; CHAMOMILE; CITRUS BIOFLAVONOIDS; GLYCERIN; GREEN TEA LEAF; LONICERA JAPONICA FLOWER; LECITHIN, SOYBEAN; LICORICE; AZADIRACHTA INDICA SEED OIL; MAHONIA AQUIFOLIUM ROOT; ALCOHOL; RICE BRAN; WATER; SILICON DIOXIDE; SUCROSE COCOATE; SUNFLOWER OIL; XANTHAN GUM

Eczema Symptom Relief

ACTIVE INGREDIENT

Drug Facts__________________________________________________________________________________________________________

HPUS active ingredient Purpose†

Equal volumes of each active ingredient in 10X, 20X, and 30X potencies, unless otherwise noted.

Active ingredients 50% of total weight.

Cardiospermum* (2X, 10X, 20X, 30X), Hydrastis canadensis*, Hydrastis canadensis*, Lappa major*, Rhus tox*, Rumex crispus*, Ruta graveolens*, Sanguinaria canadensis*, Taraxacum officinale*.

*Certified organic Ingredient

**"HPUS"indicates the active ingredients are in the official Homeopathic Pharmacopoeia of the United States.

INDICATIONS AND USAGE

Uses for temporary relief of eczema: •redness •intense itching •allergic skin eruptions •dry or moist eruptions •thickened, crusty, scaly skin •inflamed skin •general unhealthy skin

Warnings

- For external use only. Avoid contact with eyes and broken skin.
- Stop use and ask a doctor if •increased skin irritation or other allergic reaction develops. •symptoms worsen or do not improve within 7 days.
- Nursing mothers should not apply to breast area.
- Keep out of reach of children.
- If swallowed, get medical help or contact a Poison Control Center immediately.

- Keep out of reach of children.

Directions

•Shake before using. •Adults & children 2 years of age and older: apply to affected area up to 4 times daily. Rub in gently. •Children under 2 years of age: consult a doctor. •Patch test recommended on sensitive skin.

Other information:

- To open: unscrew cap, remove tube seal, replace cap.
- Safety sealed for your protection.
- Do not use if tube seal is missing.
- Store at 68-77° (20-25°C).
- Certified organic topical lotion.

INACTIVE INGREDIENT

Inactive ingredients: Aloe vera leaf juice powder*, avena sativa oat kernel flour*, carrageenan, chamomile recutita flower extract*, citrus extract*, glycerin, green tea extract*, honeysuckle extract*, lecithin*, licorice root extract*, neem seed oil*, oregon grape root extract*, organic alcohol*, oryza sativa race bran extract*, silicon dioxide, sucrose cocoate, sunflower oil*, water, xanthan gum.

*Certified organic Ingredient.

Certified organic by Oregon Tilth.

PURPOSE

__________________________________________________________________________________________________________

HPUS active ingredient Purpose†

Equal volumes of each active ingredient in 10X, 20X, and 30X potencies, unless otherwise noted.

Active ingredients 50% of total weight.

Cardiospermum (2X, 10X, 20X, 30X)......................................................allergic skin eruption

Hydrastis canadensis..............................................................general unhealthy skin, eczema

Hydrocotyle asiatica.................................dry, eruptions, thickening of skin, exfoliation of scales

Lappa major...................................................................moist eruptions, greyish white crusts

Rhus tox........................................red, swollen, burning eczematous eruptions, scale formation

Rumex crispus.................................................................................intense itching, skin rash

Ruta graveolens......................................................................itching, inflamed, deep red skin

Sanguinaria canadensis...........................................................................redness and burning

Taraxacum officinale....................................................severe itching, skin rash, unhealthy skin